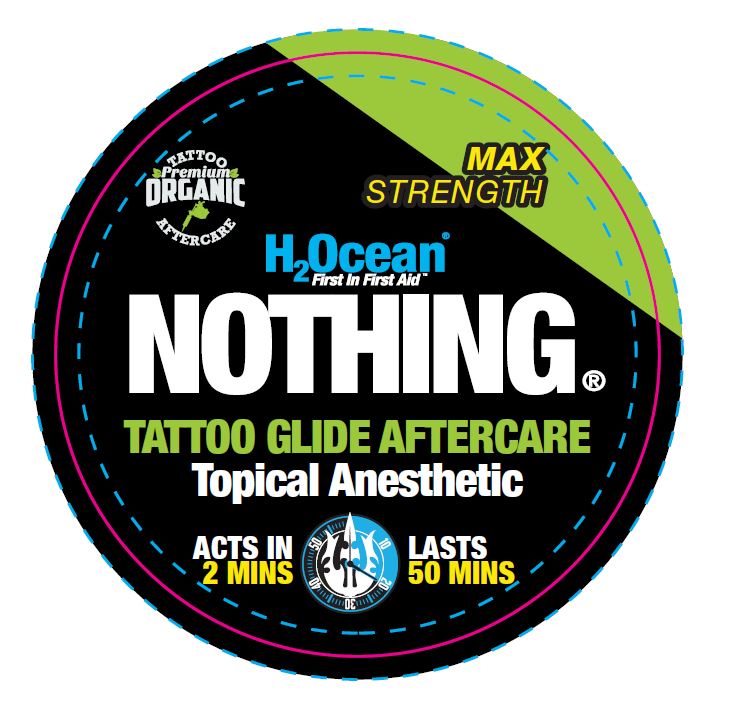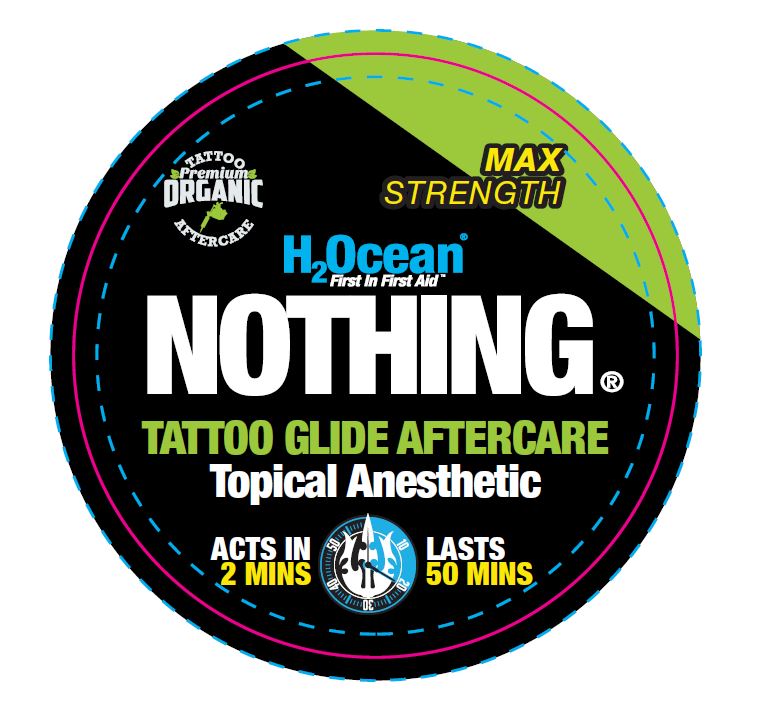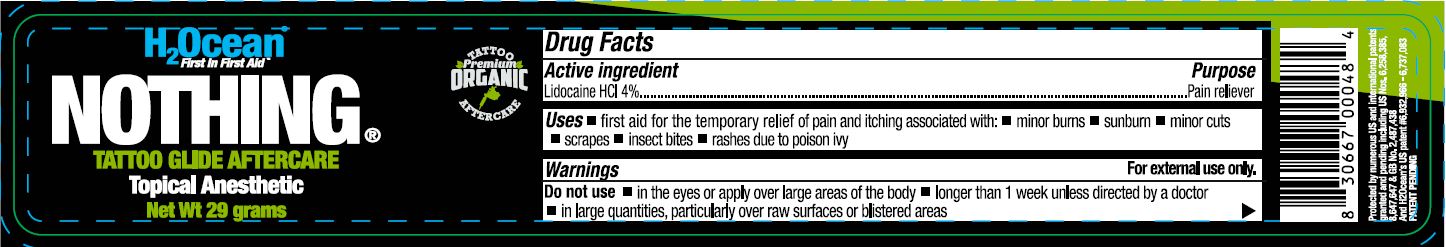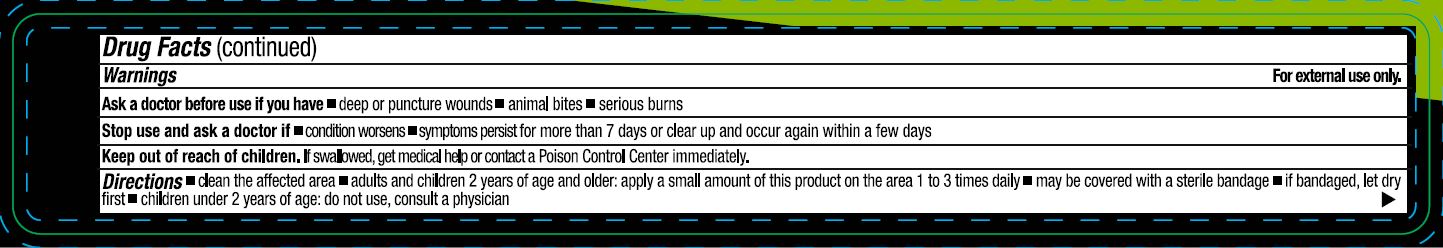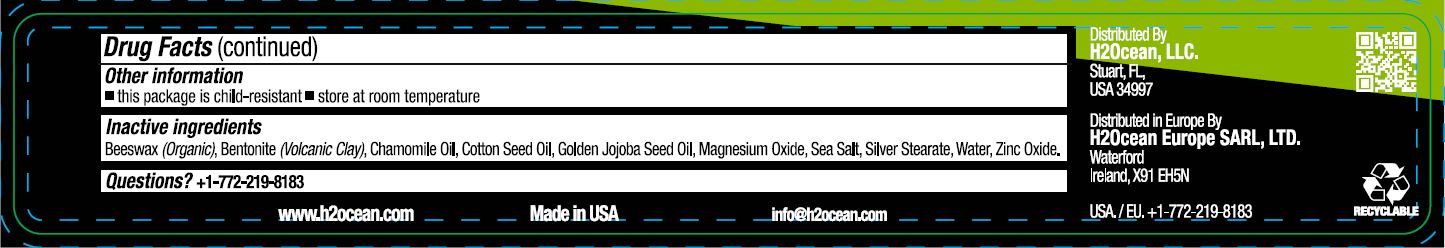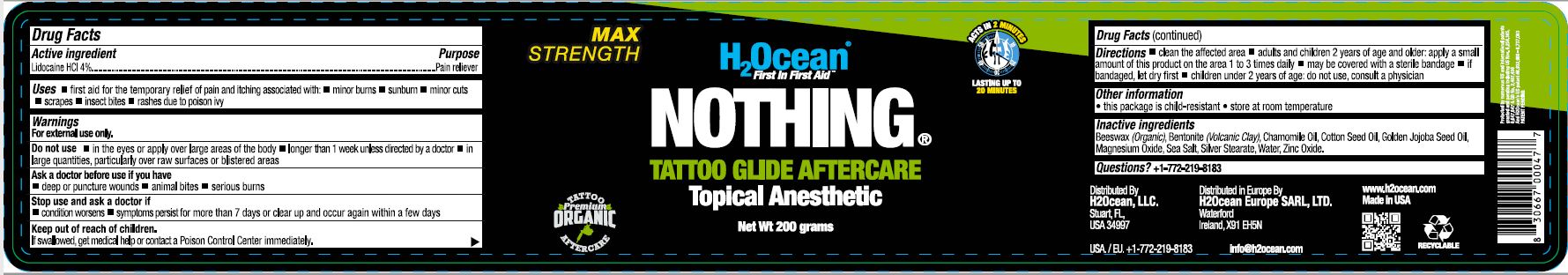 DRUG LABEL: H2Ocean NOTHING TATTOO GLIDE AFTERCARE
NDC: 70411-200 | Form: OINTMENT
Manufacturer: H2Ocean, LLC
Category: otc | Type: HUMAN OTC DRUG LABEL
Date: 20250625

ACTIVE INGREDIENTS: LIDOCAINE 4 g/100 g
INACTIVE INGREDIENTS: WATER; ZINC OXIDE; MAGNESIUM OXIDE; SEA SALT; YELLOW WAX; COTTONSEED OIL; BENTONITE; JOJOBA OIL; SILVER STEARATE; CHAMOMILE FLOWER OIL

70411-200 H2Ocean NOTHING TATTOO GLIDE AFTERCARE

Active ingredient

Lidocaine HCL 4%

Purpose

Pain reliever

Uses

First aid for temporary relief of pain and itching associated with: • minor burns • sunburn • minor cuts • scrapes • insect bites • rashes due to poison ivy

Warnings

For external use only.
Do not use • in the eyes or apply over large areas of the body • longer than 1 week unless directed by a doctor •in large quantities, particularly over raw surfaces or blistered areas
Ask a doctor before use if you have
• deep or puncture wounds • animal bites • serious burns
Stop use and ask a doctor if
• condition worsens • symptoms persist for more than 7 days or clear up and occur again within a few days

Keep out of reach of children.

OTHER SAFETY INFORMATION

If swallowed, get medical help or contact a Poison Control Center immediately.

Directions

• clean the affected area • adults and children 2 years of age and older: apply a small amount of this product on the area 1 to 3 times daily • may be covered with a sterile bandage • if bandaged, let dry first • children under 2 years of age: do not use, consult a physician

Inactive ingredients

Beeswax (Organic), Bentonite (Volcanic Clay), Chamomile Oil, Cotton Seed Oil, Golden Jojoba Seed Oil, Magnesium Oxide, Sea Salt, Silver Stearate, Water, Zinc Oxide